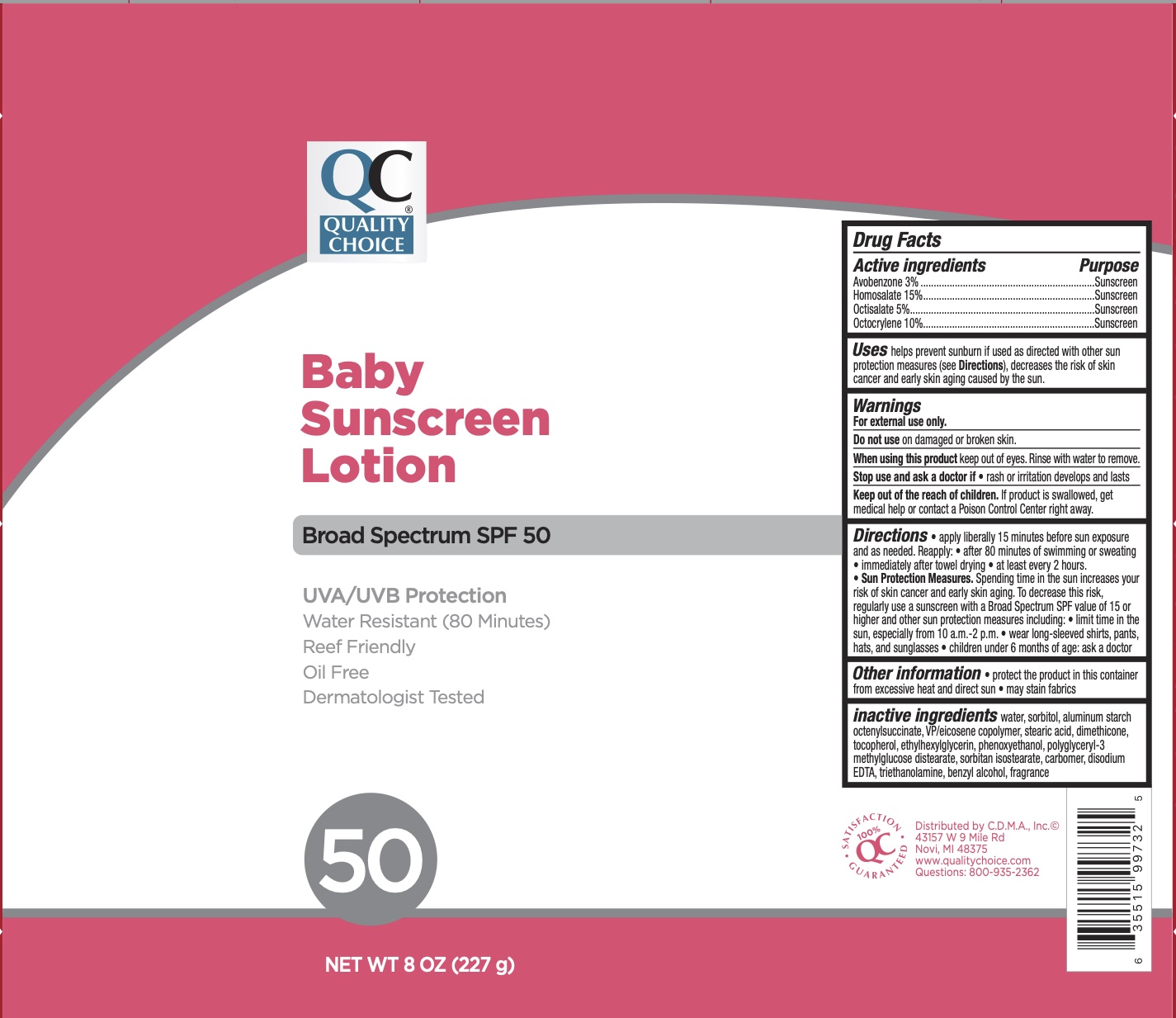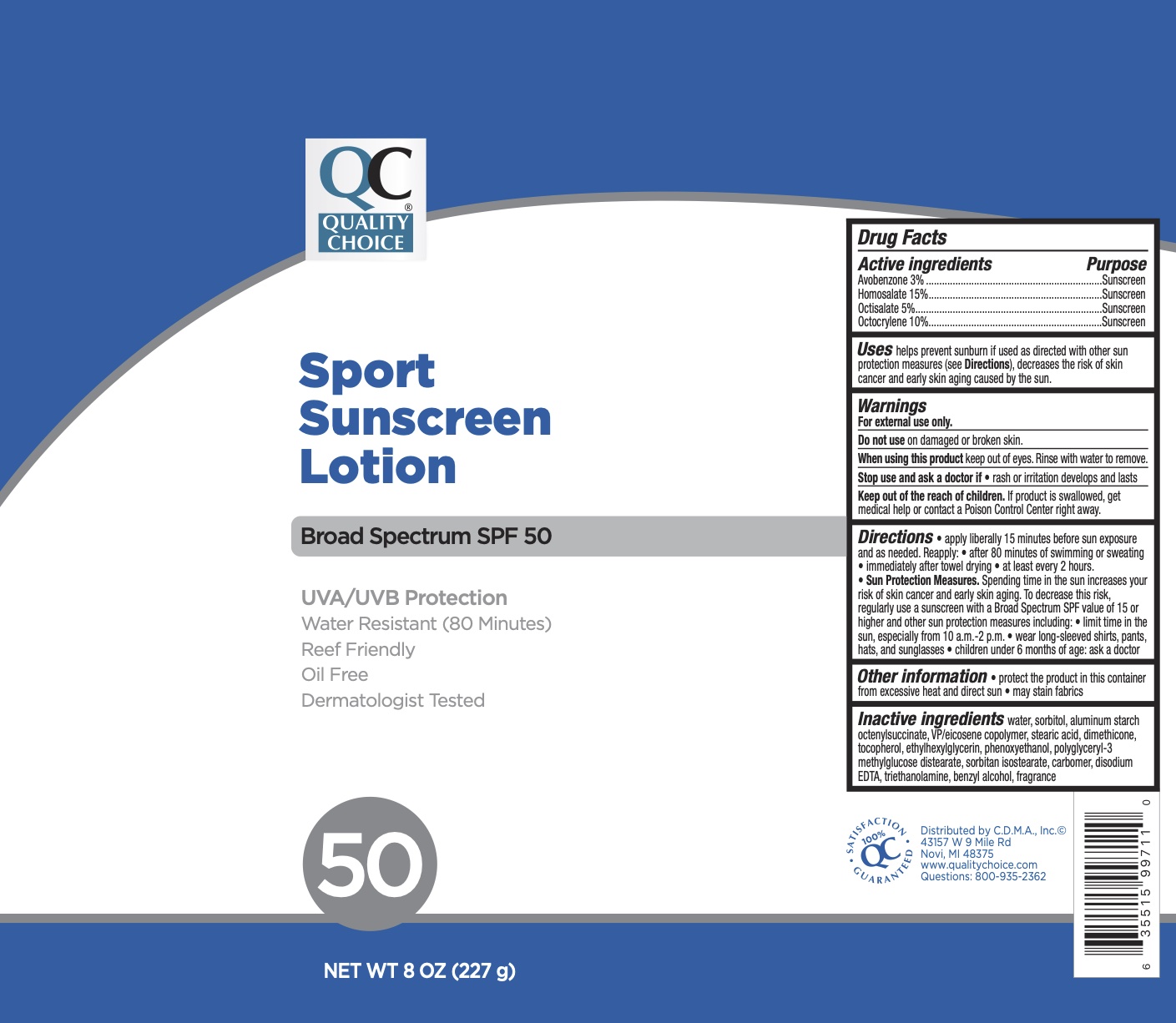 DRUG LABEL: QC SPF 50 Sunscreen
NDC: 63868-531 | Form: LOTION
Manufacturer: CDMA
Category: otc | Type: HUMAN OTC DRUG LABEL
Date: 20241215

ACTIVE INGREDIENTS: AVOBENZONE 3 g/100 g; OCTOCRYLENE 10 g/100 g; HOMOSALATE 15 g/100 g; OCTISALATE 5 g/100 g
INACTIVE INGREDIENTS: EICOSYL POVIDONE; ALUMINUM STARCH OCTENYLSUCCINATE; TOCOPHEROL; BENZYL ALCOHOL; ETHYLHEXYLGLYCERIN; PHENOXYETHANOL; POLYGLYCERYL-3 METHYLGLUCOSE DISTEARATE; SORBITAN ISOSTEARATE; SORBITOL; STEARIC ACID; WATER; TROLAMINE; EDETATE DISODIUM; DIMETHICONE 350; CARBOMER 940

QC SPF 50 Sunscreen Lotion

Active Ingredients

Avobenzone 3%, Homosalate 15%, Octisalate 5%, Octocrylene 10%

Purpose

Sunscreen

Uses

Helps prevent sunburn. If used as directed with other sun protection measures (see Directions), decreases the risk of skin cancer and early skin aging caused by the sun.

Warnings

For external use only.

Do not use on damaged or broken skin. When using this product keep out of eyes. Rinse eyes with water to remove.

Stop use and ask a doctor if rash occurs.

Keep Out of Reach of Children.

If swallowed, get medical help or contact a Poison Control Center right away.

Directions

Apply liberally 15 minutes before sun exposure. Reapply:

- after 80 minutes of swimming or sweating
- immediately after towel drying
- at least every 2 hours

Sun protection measures: spending time n the sun increases your risk of skin cancer and early skin aging. To decrease risk, regularly use a sunscreen with broad spectrum SPF of 15 or higher and other sun protection measure including:

- limit time in the sun, especially from 10 am to 2 pm
- wear long-sleeved shirts, pants, hats, and sunglasses.
- Children under 6 months: ask a doctor.

Inactive Ingredients

Water, sorbitol, aluminum starch octenylsuccinate, VP/eicosene copolymer, stearic acid, dimethicone, tocopherol, carbomer, disodium EDTA, ethylhexylglycerin, phenoxyethanol, polyglyceryl-3 methylglucose distearate, sorbitan isostearate, benzyl alcohol, triethanolamine, fragrance.